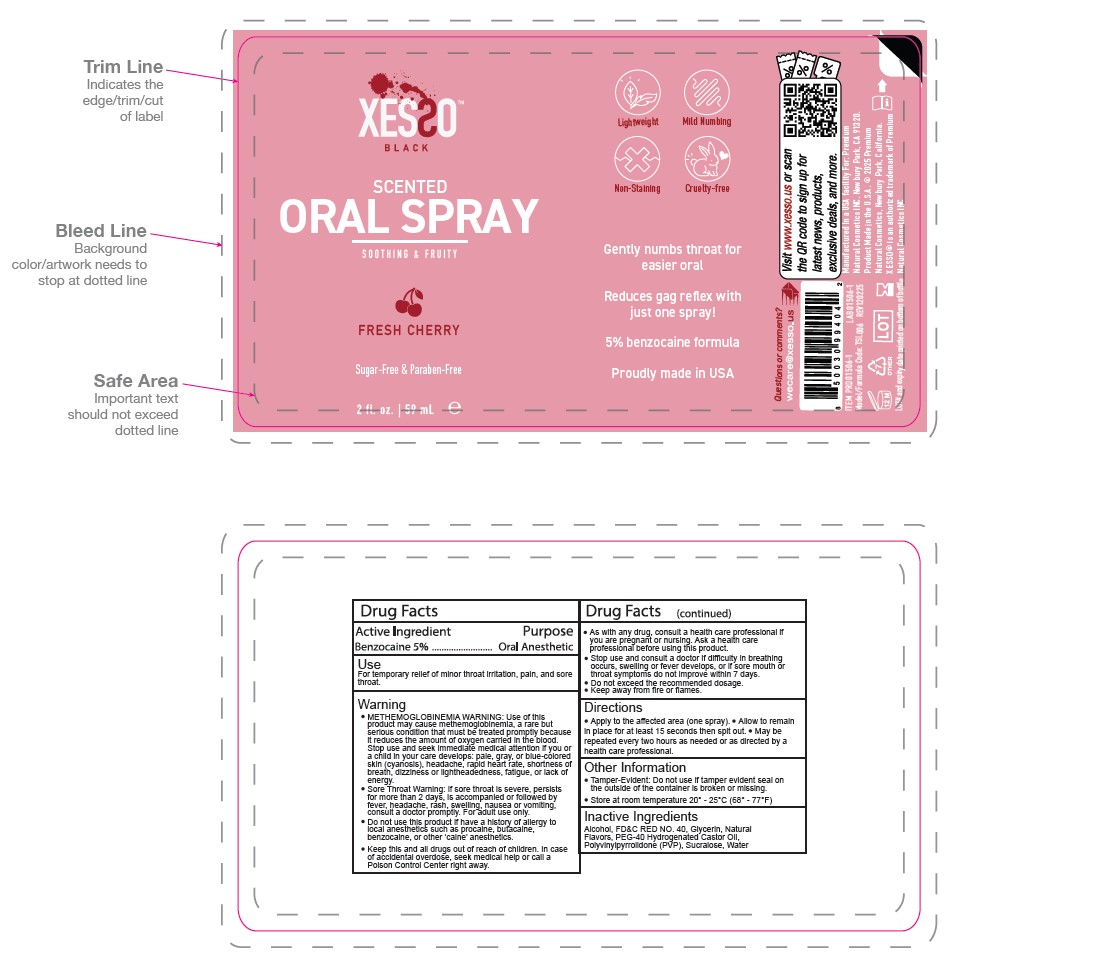 DRUG LABEL: Xesso Neo
NDC: 81777-106 | Form: SPRAY
Manufacturer: PREMIUM NATURAL COSMETICS INC
Category: otc | Type: HUMAN OTC DRUG LABEL
Date: 20251017

ACTIVE INGREDIENTS: BENZOCAINE 5 g/100 mL
INACTIVE INGREDIENTS: POVIDONE, UNSPECIFIED; POLYOXYL 40 CASTOR OIL; SUCRALOSE; FD&C RED NO. 40; GLYCERIN; WATER; ALCOHOL 95%

Xesso Neo 5% Benzocaine Oral Spray

Warning

- METHEMOGLOBINEMIA WARNING: Use of this product may cause methemoglobinemia, a rare but serious condition that must be treated promptly because it reduces the amount of oxygen carried in the blood. Stop use and seek immediate medical attention if you or a child in your care develops: pale, gray, or blue-colored skin (cyanosis), headache, rapid heart rate, shortness of breath, dizziness or lightheadedness, fatigue, or lack of energy.
- Sore Throat Warning: If sore throat is severe, persists for more than 2 days, is accompanied or followed by fever, headache, rash, swelling, nausea or vomiting, consult a doctor promptly. For adult use only.
- Do not use this product if you have a history of allergy to local anesthetics such as procaine, butacaine, benzocaine, or other ‘caine’ anesthetics.
- Keep this and all drugs out of reach of children. In case of accidental overdose, seek medical help or call a Poison Control Center right away.
- As with any drug, consult a health care professional if you are pregnant or nursing. Ask a health care professional before using this product.
- Stop use and consult a doctor if difficulty in breathing occurs, swelling or fever develops, or if sore mouth or throat symptoms do not improve within 7 days.
- Do not exceed the recommended dosage.
- Keep away from fire or flames.

Keep out of reach of children section

Keep this and all drugs out of reach of children. In case of accidental overdose, seek medical help or call a Poison Control Center right away.

Directions

Apply to the affected area (one spray).
Allow to remain in place for at least 15 seconds then spit out.
May be repeated every two hours as needed or as directed by a health care professional.

Inactive Ingredients

Alcohol, FD&C RED NO. 40, Glycerin, Natural Flavors, PEG-40 Hydrogenated Castor Oil, Polyvinylpyrrolidone (PVP), Sucralose, Water.

Use Section

For temporary relief of minor throat irritation, pain, and sore throat.

Active Ingredient

Benzocaine 5%

Purpose

Oral Anesthetic

Other Information

Tamper-Evident: Do not use if tamper evident seal on the outside of the container is broken or missing.
Store at room temperature 20 - 25 C (68 - 77 F)